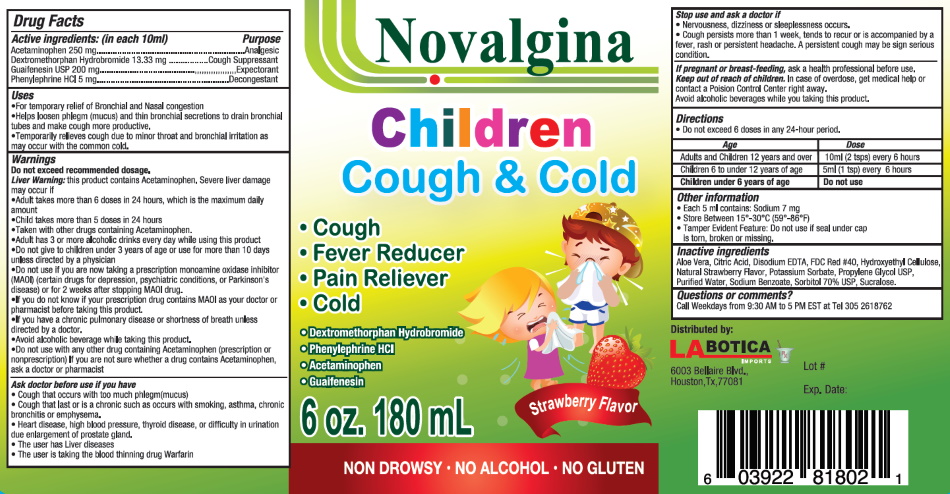 DRUG LABEL: Novalgina
NDC: 83057-0001 | Form: LIQUID
Manufacturer: HBC Pharma, LLC
Category: otc | Type: HUMAN OTC DRUG LABEL
Date: 20241104

ACTIVE INGREDIENTS: ACETAMINOPHEN 250 mg/10 mL; DEXTROMETHORPHAN HYDROBROMIDE 13.33 mg/10 mL; GUAIFENESIN 200 mg/10 mL; PHENYLEPHRINE HYDROCHLORIDE 5 mg/10 mL
INACTIVE INGREDIENTS: CITRIC ACID MONOHYDRATE; EDETATE DISODIUM; FD&C RED NO. 40; HYDROXYETHYL CELLULOSE (100 MPA.S AT 2%); PROPYLENE GLYCOL; WATER; SODIUM BENZOATE; SORBITOL; SUCRALOSE; ALOE VERA LEAF

Novalgina Children Cough and Cold

Active Ingredients:(in each 10 ml.) | Purpose
Acetaminophen 250 mg ........................................................ | Analgesic
Dextromethorphan Hydrobromide 13.33 mg ....................... | Cough Suppressant
Guaifenesin USP 200 mg...................................................... | Expectorant
Phenylephrine HCl 5 mg....................................................... | Decongestant

Uses:

- For temporary relief og Bronchial and Nasal congestion
- Helps loosen phlegm (mucus) and thin bronchial secretions to drain bronchial tubes and make cough more productive.
- Temporarily relieves cough due to minor throat and bronchial irritation as may occur with the common cold.

Warnings

Do not exceed recommended dosage

Liver Warning this product contatins Acetaminophen. Severe liver damage may occur if

DO NOT USE

- Adult takes more than 6 doses in 24 hours, which is the maximum daily amount
- Child takes more than 5 doses in 24 hours
- Taken with other drugs containing Acetaminophen.
- Adult has 3 or more alcoholic drinks every day while using this product
- Do not give to children under 3 years of age or use for more than 10 days unless directed by a physician
- Do not use if you are now taking a prescription monoamine oxidase inhibitor (MAOI) (certain drugs for depression, psychiatric conditions, or Parkinson's disease) or for 2 weeks after stopping MAOI drug.
- If you do not know if your prescription drug contains MAOI as your doctor or pharmacist before taking this product.
- If you have a chronic pulmonary disease or shortness of breath unless directed by a doctor.
- Avoid alcoholic beverage while taking this product.
- Do not use with any other drug containing Acetaminophen (prescription no nonprescription) If you are not sure whether a drug contains Acetaminophen, ask a doctor or pharmacist

Stop use and ask a doctor

- Nervousness, dizziness or sleeplessness occurs.
- Cough persists more than 1 week, tends to recur or is accompanied by a fever, rash or persistent headache. A persistent cough may be signserious condition.

Ask doctor before use if you have

- Cough that occurs with too much phlegm(mucus)
- Cough that last or is a chronic such as occurs with smoking, asthma, chronic bronchitis or emphysema.
- Heart disease, high blood pressure, thyroid disease, or difficulty in urination due enlargement of prostate gland.
- The user has Liver diseases
- The user us taking the blood thinning drug Warfarin

PREGNANCY OR BREAST FEEDING

If pregnant or breast-feeding ask a health professional before use.

Keep out of reach of children.

In case of overdose, get medical help or contact a Poison Control Center right away.

Directions

- Do not exceed 6 doses in any 24-hour period.

AGE | DOSE
Adults and Children 12 years and over | 10 ml (2 tsps) every 6 hours
Children 6 to under 12 years of age | 5 ml (1 tsp) every 6 hours
Children under 6 years of age | Do not use

Other Information:

- Each 10 mls contains: sodium 4 mg
- Store between 15 - 30 degrees Celsius (59 - 86 Fahrenheit).
- Tamper Evident Feature:Do not use if seal under cap is torn, broken or missing.

Inactive Ingredient

Aloe Vera, Citric Acid, Disodium EDTA, FDC Red #40, Hydroxyethyl Cellulose, Natural Strawberry Flavor, Propylene Glycol USP, Purified Water, Sodium Benzoate, Sorbitol 70% USP, Sucralose.

Questions or Comments

Call Weekdays from 9:30 AM to 5PM EST at Tel 800-491-7908

Made in U.S.A.